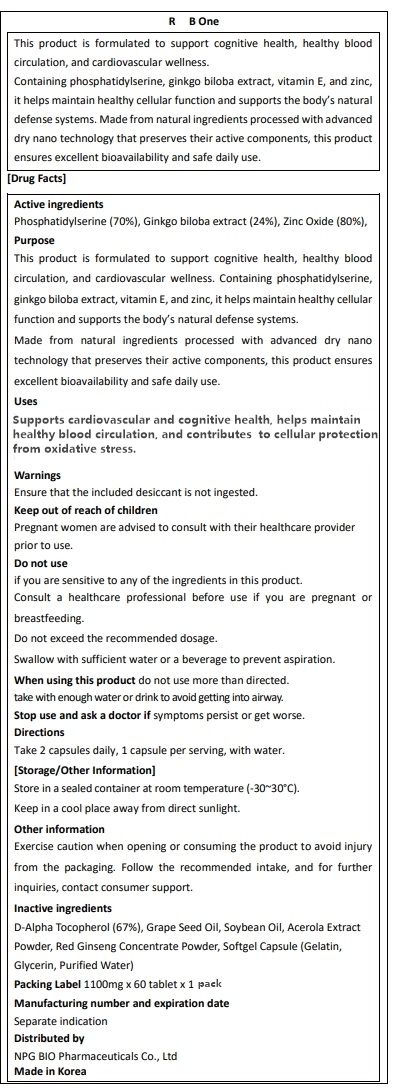 DRUG LABEL: R B one
NDC: 84540-140 | Form: TABLET
Manufacturer: NPG Bio Pharmaceuticals Co.,Ltd.
Category: otc | Type: HUMAN OTC DRUG LABEL
Date: 20251218

ACTIVE INGREDIENTS: ZINC OXIDE 6.38 mg/1100 mg; PHOSPHATIDYL SERINE 214 mg/1100 mg; GINKGO BILOBA LEAF 75.02 mg/1100 mg
INACTIVE INGREDIENTS: .ALPHA.-TOCOPHEROL, D-; GRAPE SEED OIL; ASIAN GINSENG; GELATIN; GLYCERIN; MALPIGHIA GLABRA (ACEROLA) FRUIT; WATER; SOYBEAN OIL

84540-140-01 R B one ptp

Active Ingredients

Phosphatidylserine 70% 214.39 mg
Ginkgo biloba ext. 24% 75.02 mg
Zinc Oxide 80% 6.38 mg

Purposes

This product is formulated to support cognitive health, healthy blood circulation, and cardiovascular wellness. Containing phosphatidylserine, ginkgo biloba extract, vitamin E, and zinc, it helps maintain healthy cellular function and supports the body’s natural defense systems. Made from natural ingredients processed with advanced dry nano technology that preserves their active components, this product ensures excellent bioavailability and safe daily use.

Uses

Supports healthy blood circulation, cognitive function, and cardiovascular wellness.

Warnings

Do not use if you are sensitive to any of the ingredients in this product. Consult a healthcare professional before use if you are pregnant or breastfeeding.
Do not exceed the recommended dosage.
Swallow with sufficient water or a beverage to prevent aspiration.

Warnings

Keep out of reach of children
Pregnant women are advised to consult with their healthcare provider prior to use.

Warnings

Stop use and ask a doctor if symptoms persist or get worse.

Warnings

When using this product do not use more than directed.

take with enough water or drink to avoid getting into airway.

Warnings

Ensure that the included desiccant is not ingested.

Directions

Take 2 Capsuel daily, 1 capsule per serving, with water.

Inactive Ingredients

D-Alpha Tocopherol (67%)

Grape Seed Oil

Soybean Oil

Acerola Extract Powder

Red Ginseng Concentrate Powder

Softgel Capsule (Gelatin, Glycerin, Purified Water)